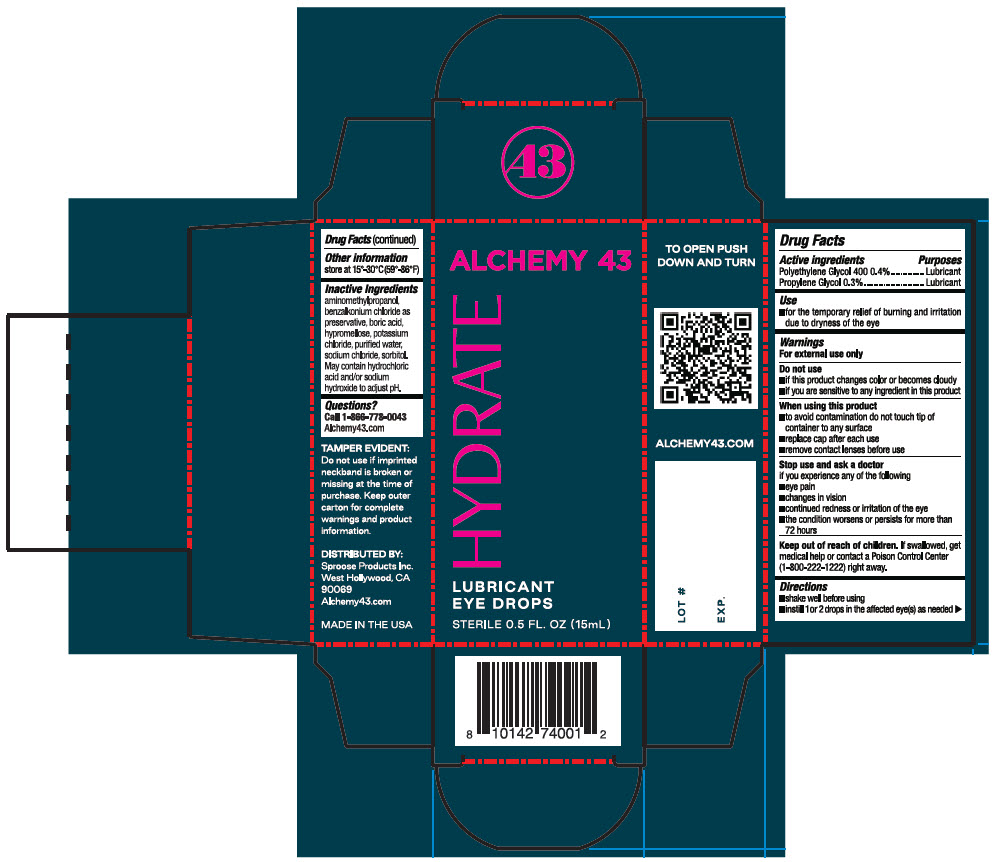 DRUG LABEL: HYDRATE Lubricant
NDC: 83716-6000 | Form: SOLUTION/ DROPS
Manufacturer: Sproose Products Inc.
Category: otc | Type: HUMAN OTC DRUG LABEL
Date: 20240308

ACTIVE INGREDIENTS: POLYETHYLENE GLYCOL 400 0.004 g/1 mL; PROPYLENE GLYCOL 0.003 g/1 mL
INACTIVE INGREDIENTS: AMINOMETHYLPROPANOL; BENZALKONIUM CHLORIDE; BORIC ACID; HYPROMELLOSE, UNSPECIFIED; POTASSIUM CHLORIDE; WATER; SODIUM CHLORIDE; SORBITOL

HYDRATE Lubricant

Drug Facts

ACTIVE INGREDIENT

PURPOSE

Active Ingredients | Purposes
Polyethylene glycol 400 0.04% | Lubricant
Propylene glycol 0.3% | Lubricant

Uses

- for the temporary relief of burning and irritation due to dryness of the eye

Warnings

For external use only

Do not use

- if this product changes color or becomes cloudy
- if you are sensitive to any ingredient in this product

When using this product

- to avoid contamination do not touch tip of container to any surface
- replace cap after each use
- remove contacts before using

Stop use and ask a doctor if you experience any of the following

- eye pain
- changes in vision
- continued redness or irritation of the eye
- the condition worsens or persists for more than 72 hours

Keep out of reach of children. If swallowed, get medical help or contact a Poison Control Center (1-800-222-1222) right away.

Directions

- shake well before using
- Instill 1 or 2 drops in the affected eye(s) as needed

Other information

store at 15°-30°C (59°-86°F)

Inactive Ingredients

Aminomethylpropanol, benzalkonium chloride as preservative, boric acid, hypromellose, potassium chloride, purified water, sodium chloride, sorbitol. May contain hydrochloric acid and/or sodium hydroxide to adjust pH.

Questions?

866-778-0043 Alchemy43.com

Distributed by
Sproose Products Inc.
West Hollywood, CA

PRINCIPAL DISPLAY PANEL - 15 mL Bottle Carton

ALCHEMY 43

HYDRATE

LUBRICANT
EYE DROPS

STERILE 0.5 FL. OZ (15mL)